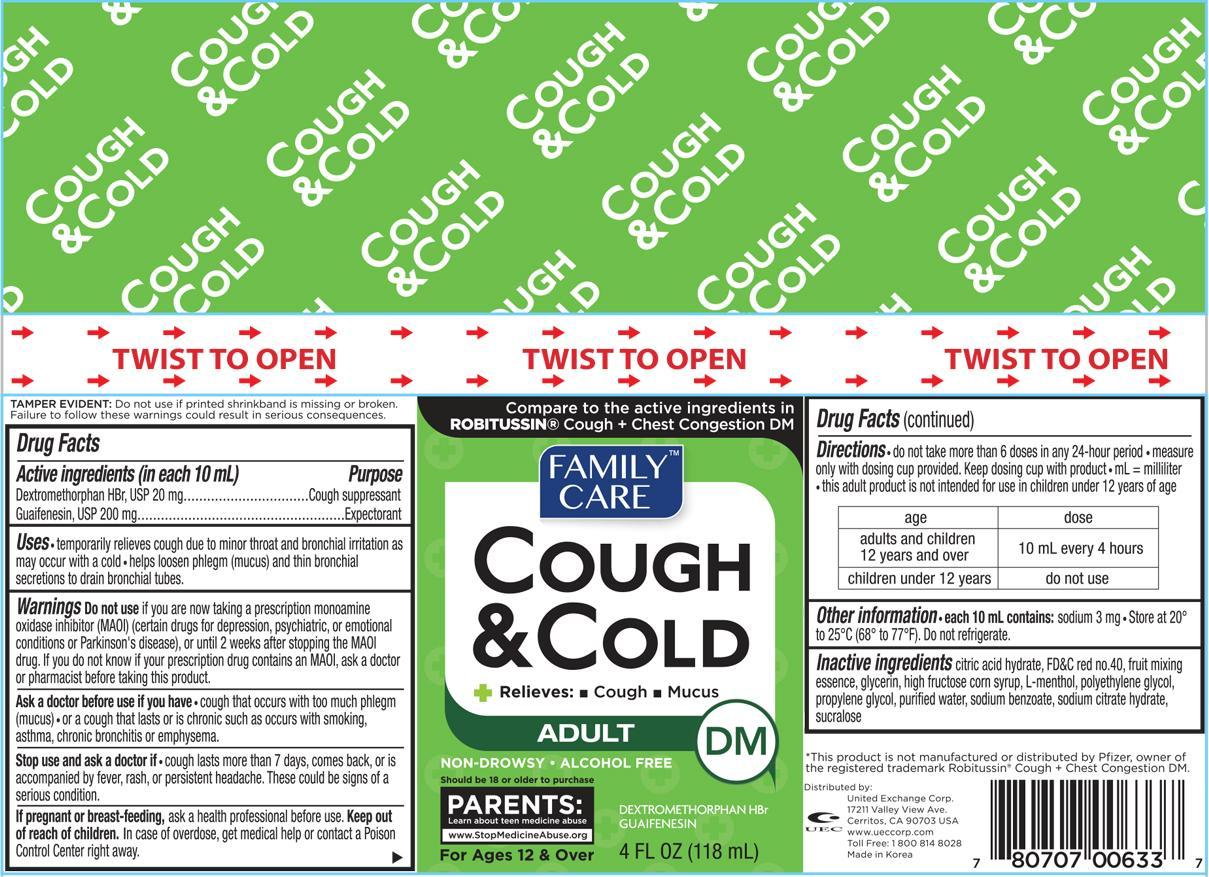 DRUG LABEL: Family Care Cough and Cold
NDC: 65923-633 | Form: LIQUID
Manufacturer: United Exchange Corp.
Category: otc | Type: HUMAN OTC DRUG LABEL
Date: 20150729

ACTIVE INGREDIENTS: DEXTROMETHORPHAN HYDROBROMIDE 40 mg/10 mL; GUAIFENESIN 400 mg/10 mL
INACTIVE INGREDIENTS: FD&C RED NO. 40; GLYCERIN; HIGH FRUCTOSE CORN SYRUP; MENTHOL; POLYETHYLENE GLYCOLS; PROPYLENE GLYCOL; WATER; SODIUM BENZOATE; SUCRALOSE

Active ingredients (in each 10 mL) Purpose

Dextromethorphan HBr, USP 20 mg............................................Cough suppressant

Guaifenesin, USP 200 mg....................................................................Expectorant

Uses

- temporarily relieves cough due to minor throat and bronchial irritation as may occur with a cold
- helps loosen phlegm (mucus) and thin bronchial secretions to drain brnchial tubes.

Warnings

Do not use if you are now taking a prescription monoamine oxidase inhibitor (MAOI) (certain drugs for depression, psychiatric, or emotional conditions or Parkinson's disease), or until 2 weeks after stopping the MAOI drug. If you do not know if your prescription drug contains an MAOI, ask a doctor or pharmacist before taking this product.

Ask a doctor before use if you have

- cough that occurs with too much phlegm (mucus)
- or a cough that lasts or is chronic such as occurs with smoking, asthma, chronic bronchitis or emphysema.

Stop use and ask a doctor if

- cough lasts more than 7 days, comes back, or is accompanied by fever, rash, or persistent headache. These could be signs of a serious condition.

PREGNANCY OR BREAST FEEDING

If pregnant or breast-feeding, ask a health professional before use.

Keep out of reach of children. In case of overdose, get medical help or contact a Poison Control Center right away.

Directions

- do not take more than 6 doses in any 24-hour period
- measure only with dosing cup provided. Keep dosing cup with product
- mL = milliliter
- this adult product is not intended for use in children under 12 years of age

age | dose
adults and children 12 years and over | 10 mL every 4 hours
children under 12 years | do not use

Other information

- each 10 mL contains: sodium 3 mg
- Store at 20° to 25°C (68° to 77°F). Do not refrigerate.

Inactive ingredients

citric acid hydrate, FD&C red no. 40, fruit mixing essence, glycerin, high fructose corn syrup, L-menthol, polyethylene glycol, propylene glycol, purified water, sodium benzoate, sodium citrate hydrate, sucralose

DOSAGE AND ADMINISTRATION

Distributed by:

United Exchange Corp.

17211 Valley View Ave.

Cerritos, CA 90703 USA

Made in Korea